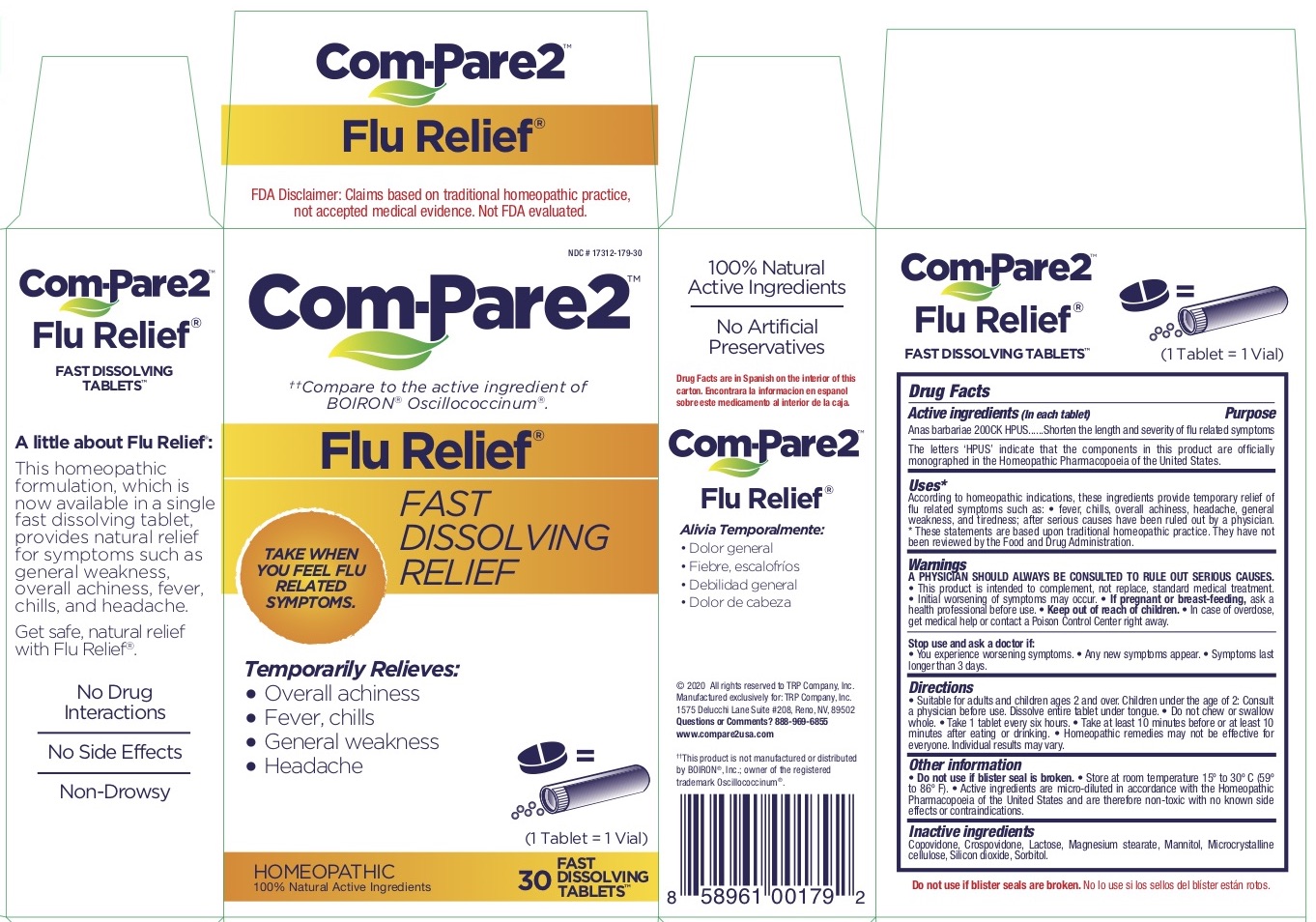 DRUG LABEL: Com-Pare2 Flu Relief
NDC: 17312-179 | Form: TABLET
Manufacturer: TRP Company
Category: homeopathic | Type: HUMAN OTC DRUG LABEL
Date: 20251215

ACTIVE INGREDIENTS: CAIRINA MOSCHATA HEART/LIVER AUTOLYSATE 200 [hp_C]/1 1
INACTIVE INGREDIENTS: SILICON DIOXIDE; LACTOSE, UNSPECIFIED FORM; MANNITOL; CROSPOVIDONE; MAGNESIUM STEARATE; MICROCRYSTALLINE CELLULOSE; SORBITOL; COPOVIDONE K25-31

Com-Pare2 Flu Relief

Active Ingredient

Anas barbariae 200CK

Purpose

Anas barbariae ......Shorten the length and severity of flu related symptoms

Inactive Ingredients

Copovidone, Crospovidone, Lactose, Magnesium stearate, Mannitol, Microcrystalline

cellulose, Silicon dioxide, Sorbitol.

Uses*

According to homeopathic indications, these ingredients provide temporary relief of
flu related symptoms such as: • fever, chills, overall achiness, headache, general
weakness, and tiredness; after serious causes have been ruled out by a physician.
* These statements are based upon traditional homeopathic practice. They have not
been reviewed by the Food and Drug Administration.

Warnings

A PHYSICIAN SHOULD ALWAYS BE CONSULTED TO RULE OUT SERIOUS CAUSES.
• This product is intended to complement, not replace, standard medical treatment.
• Initial worsening of symptoms may occur. • If pregnant or breast-feeding, ask a
health professional before use. • Keep out of reach of children. • In case of overdose,
get medical help or contact a Poison Control Center right away.

• Keep out of reach of children. • In case of overdose,
get medical help or contact a Poison Control Center right away.

• If pregnant or breast-feeding, ask a
health professional before use.

Stop use and ask a doctor if:

• You experience worsening symptoms. • Any new symptoms appear. • Symptoms last
longer than 3 days.

Directions

• Suitable for adults and children ages 2 and over. Children under the age of 2: Consult
a physician before use. Dissolve entire tablet under tongue. • Do not chew or swallow
whole. • Take 1 tablet every six hours. • Take at least 10 minutes before or at least 10
minutes after eating or drinking. • Homeopathic remedies may not be effective for
everyone. Individual results may vary.

• Do not use if blister seal is broken.

• Store at room temperature 15º to 30º C (59º
to 86º F).

Other Information

• Active ingredients are micro-diluted in accordance with the Homeopathic
Pharmacopoeia of the United States and are therefore non-toxic with no known side
effects or contraindications.